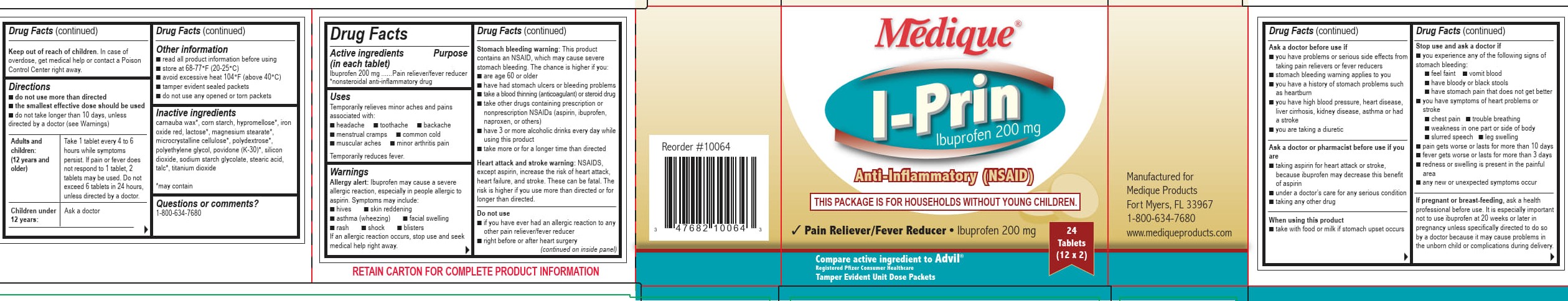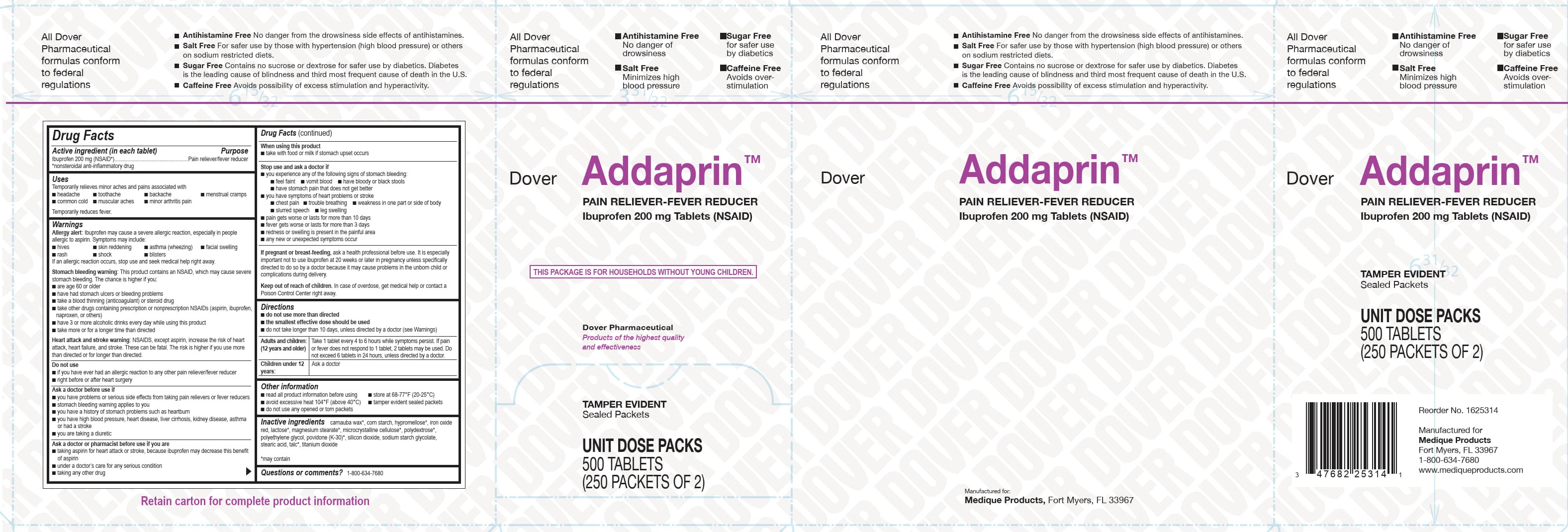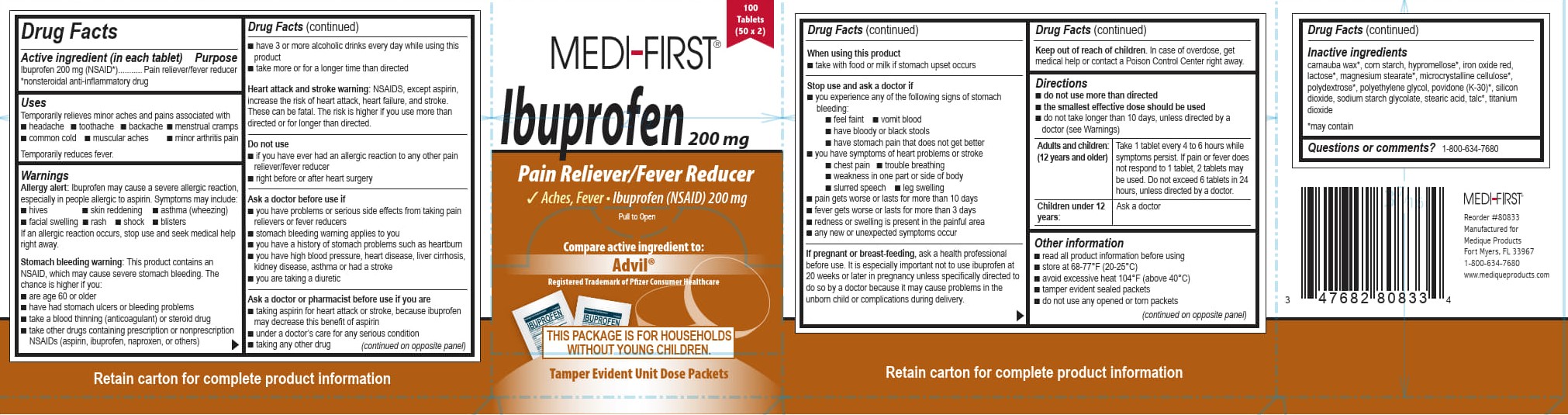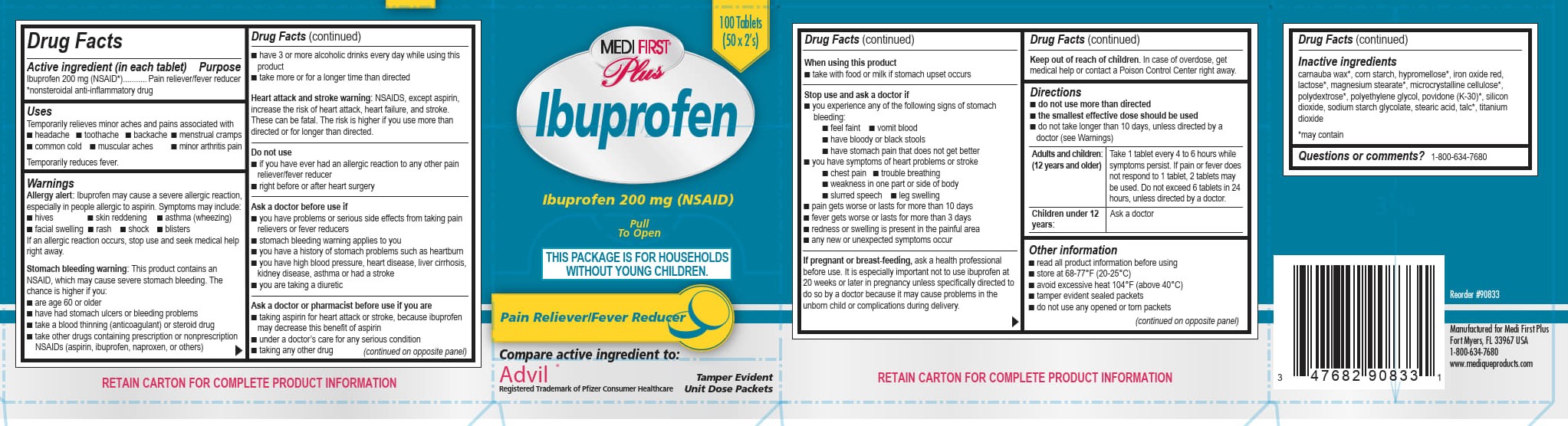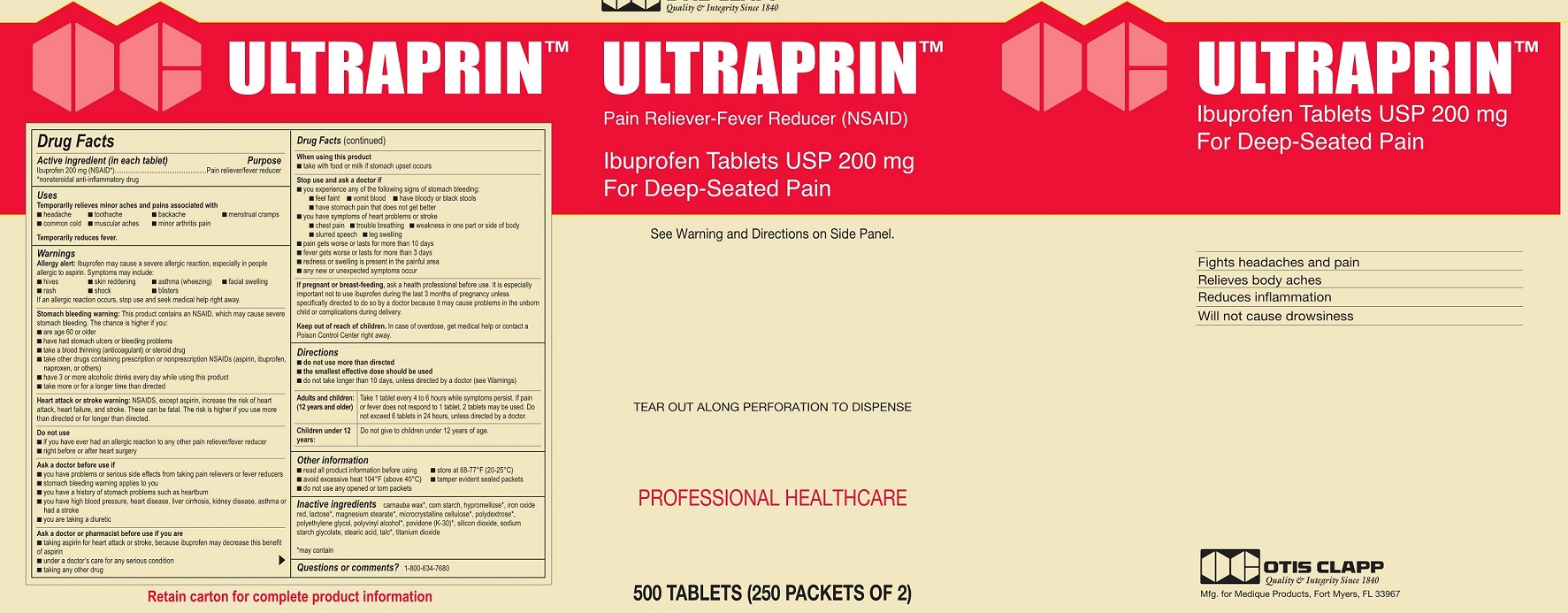 DRUG LABEL: Medique Iprin
NDC: 47682-600 | Form: TABLET, FILM COATED
Manufacturer: Unifirst First Aid Corporation
Category: otc | Type: HUMAN OTC DRUG LABEL
Date: 20250909

ACTIVE INGREDIENTS: IBUPROFEN 200 mg/1 1
INACTIVE INGREDIENTS: CARNAUBA WAX; MAGNESIUM STEARATE; SODIUM STARCH GLYCOLATE TYPE A POTATO; STEARIC ACID; TITANIUM DIOXIDE; STARCH, CORN; HYPROMELLOSES; SILICON DIOXIDE; FERRIC OXIDE RED; LACTOSE; CELLULOSE, MICROCRYSTALLINE; POLYDEXTROSE; POLYETHYLENE GLYCOL, UNSPECIFIED

UniFirst First Aid Ibuprofen

Drug Facts

Active ingredient

Ibuprofen 200 mg (NSAID*)

*nonsteroidal anti-inflammatory drug

Purpose

Pain reliever/fever reducer

Uses

Temporarily relieves minor aches and pains associated with

■ headache ■ toothache ■ backache ■ menstrual cramps

■ common cold ■ muscular aches ■ minor arthritis pain

Temporarily reduces fever.

Warnings

Allergy Alert : Ibuprofen may cause a severe allergic reaction, especially in people allergic to aspirin. Symptoms may include:

■ hives ■ skin reddening ■ asthma (wheezing) ■ facial swelling ■ rash ■ shock ■ blisters

If an allergic reaction occurs, stop use and seek medical help right away.

Stomach bleeding warning:This product contains an NSAID, which may cause severe stomach bleeding. The chance is higher if you:

■ are age 60 or older

■ have had stomach ulcers or bleeding problems

■ take a blood thinning (anticoagulant) or steroid drug

■ take other drugs containing prescription or nonprescription NSAIDs (aspirin, ibuprofen, naproxen, or others)

■ have 3 or more alcoholic drinks every day while using this product

■ take more or for a longer time than directed

Heart attack or stroke warning: NSAIDS, except aspirin, increase the risk of heart attack, heart failure, and stroke. These can be fatal. The risk is higher if you use more than directed or for longer than directed.

Do not use

■ if you have ever had an allergic reaction to any other pain reliever/fever reducer

■ right before or after heart surgery

Ask a doctor before use if

■ you have problems or serious side effects from taking pain relievers or fever reducers

■ stomach bleeding warning applies to you

■ you have a history of stomach problems such as heartburn

■ you have high blood pressure, heart disease, liver cirrhosis, kidney disease, asthma or had a stroke

■ you are taking a diuretic

Ask a doctor or pharmacist before use if you are

■ taking aspirin for heart attack or stroke, because ibuprofen may decrease this benefit of aspirin

■ under a doctor’s care for any serious condition

■ taking any other drug

When using this product

■ take with food or milk if stomach upset occurs

Stop use and ask a doctor if

■ you experience any of the following signs of stomach bleeding:

■ feel faint ■ vomit blood ■ have bloody or black stools ■ have stomach pain that does not get better

■ you have symptoms of heart problems or stroke

■ chest pain ■ trouble breathing ■ weakness in one part or side of body ■ slurred speech ■ leg swelling

■ pain gets worse or lasts for more than 10 days

■ fever gets worse or lasts for more than 3 days

■ redness or swelling is present in the painful area

■ any new or unexpected symptoms occur

PREGNANCY OR BREAST FEEDING

If pregnant or breast feeding, ask a health professional before use. It is especially important not to use ibuprofen at 20 weeks or later in pregnancy unless specifically directed to do so by a doctor because it may cause problems in the unborn child or complications during delivery.

Keep out of reach of Children. In case of overdose, get medical help or contact a Poison Control Center right away.

Directions

■ do not use more than directed

■ the smallest effective dose should be used

■ do not take longer than 10 days, unless directed by a doctor (see Warnings)

Adults and children:(12 years and older)

Take 1 tablet every 4 to 6 hours while symptoms persist. If pain or fever does not respond to 1 tablet, 2 tablets may be used.
Do not exceed 6 tablets in 24 hours, unless directed by a doctor.

Children under 12 years:

Ask a doctor

Other information

■ read all product information before using

■ store at 68-77°F (20-25°C)

■ avoid excessive heat 104°F (above 40°C)

■ tamper evident sealed packets

■ do not use any opened or torn packets

Inactive ingredients

carnauba wax*, corn starch, hypromellose*, iron oxide red, lactose*, magnesium stearate*, microcrystalline cellulose*, polydextrose*, polyethylene glycol, polyvinyl alcohol*, povidone K30*, silicon dioxide, sodium starch glycolate, stearic acid, talc*, titanium dioxide

*may contain

Questions or comments? 1-800-634-7680

Medique Iprin Label

Medique® I-Prin

Ibuprofen 200 mg

Anti-inflammatory (NSAID)

This Package is for Households without Young Children.

Pain Reliever/Fever Reducer • Ibuprofen 200 mg

24 Tablets (12 x 2)

Tamper Evident Unit Dose Packets

Medi-First Ibuprofen Label

Medi-First®

Ibuprofen 200 mg

100 tablets (50 x 2)

Pain Reliever/Fever Reducer

Aches, Fever • Ibuprofen (NSAID) 200mg

Pull to Open

Compare active ingredient to: Advil®

Registered Trademark of Pfizer Consumer Healthcare

This Package is for Households without Young Children.

Tamper Evident Unit Dose Packets

Medi-First Plus Ibuprofen Label

Medi-First® Plus

Ibuprofen

250 tablets (125 x 2’s)

This Package is for Households without Young Children

Pull To Open

Ibuprofen 200 mg (NSAID)

Pain Reliever/Fever Reducer

Compare active ingredient to:

Advil®

Registered Trademark of Pfizer Consumer Healthcare

Tamper Evident Unit Dose Packets

Dover Addaprin Label

Dover Addaprin™

Pain Reliever-Fever Reducer

Ibuprofen 200 mg Tablets (NSAID)

This Package is for Households without Young Children.

Dover Pharmaceutical

Products of the highest quality and effectiveness

Tamper Evident

Sealed Packets

Unit Dose Packs

500 Tablets

(250 Packets of 2)

All Dover Pharmaceutical formulas conform to federal regulations

Antihistamine free

No danger of drowsiness

Sugar Free

for safer use by diabetics

Salt free

Minimizes high blood pressure

Caffeine Free

Avoides over stimulation

Otis Clapp Ultraprin Label

OC Otis Clapp

Quality & Integrity Since 1840

Ultraprin ™

Pain Reliever-Fever Reducer (NSAID)

Ibuprofen Tablets USP 200 mg

For Deep Seated Pain

See Warnings and Directions on Side Panel

Tear Out Along Perforation To Dispense

Professional Healthcare

500 Tablets (250 Packets of 2)